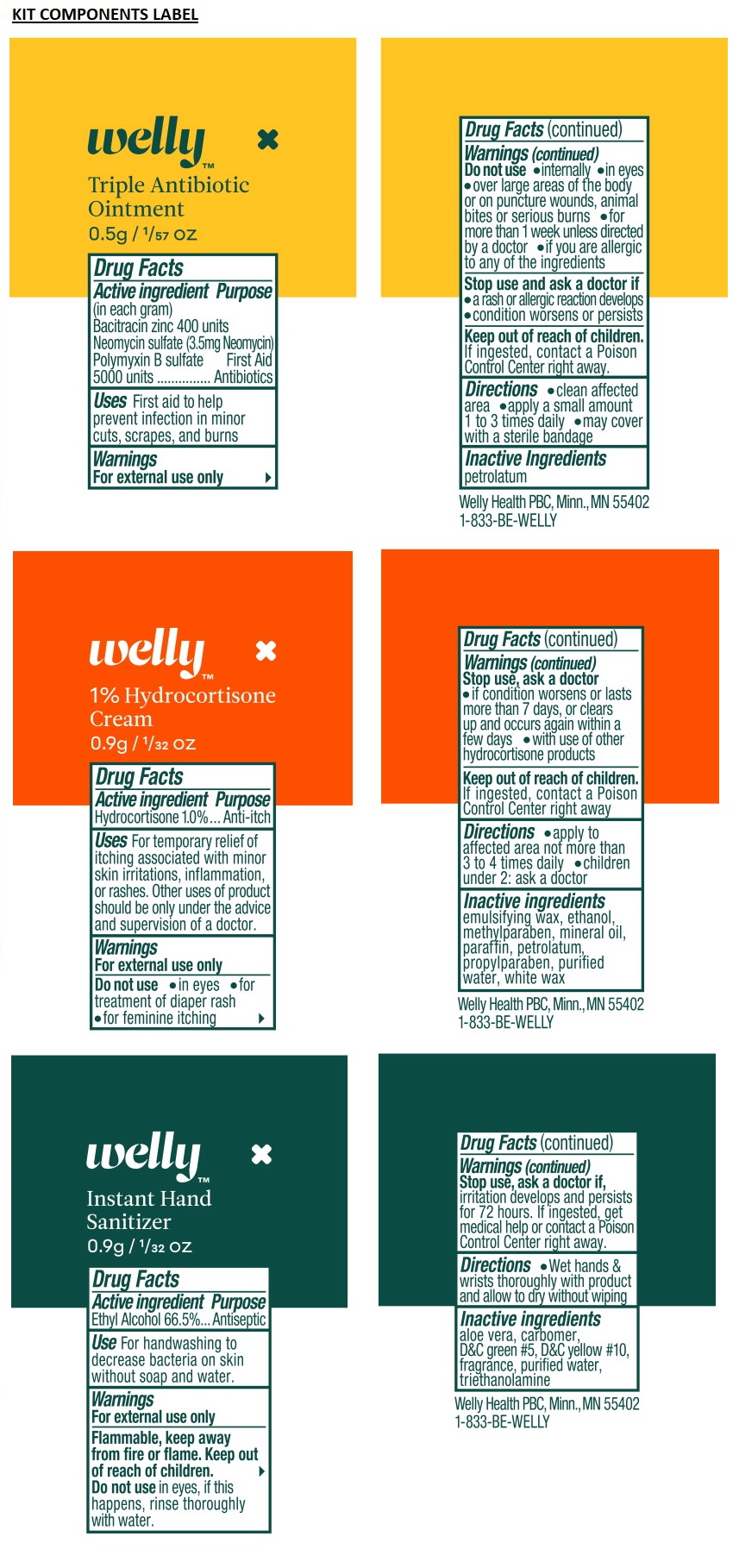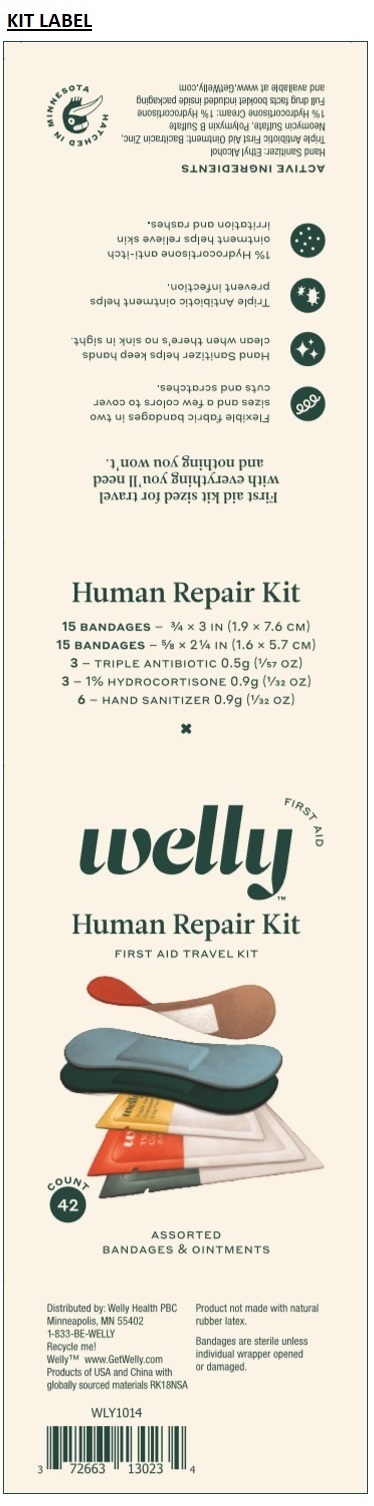 DRUG LABEL: Welly Human Repair Kit
NDC: 72663-130 | Form: KIT | Route: TOPICAL
Manufacturer: Welly Health PBC
Category: otc | Type: HUMAN OTC DRUG LABEL
Date: 20211231

ACTIVE INGREDIENTS: BACITRACIN ZINC 6 mg/1 mL; NEOMYCIN SULFATE 3.5 mg/1 mL; POLYMYXIN B SULFATE 0.77 mg/1 mL; HYDROCORTISONE 1 g/1 mL; ALCOHOL 666 mg/1 mL
INACTIVE INGREDIENTS: PETROLATUM; ALCOHOL; METHYLPARABEN; MINERAL OIL; PARAFFIN; PETROLATUM; PROPYLPARABEN; WATER; WHITE WAX; ALOE VERA LEAF; CARBOMER INTERPOLYMER TYPE A (ALLYL SUCROSE CROSSLINKED); D&C GREEN NO. 5; D&C YELLOW NO. 10; WATER; TROLAMINE

Welly Human Repair Kit

Triple Antibiotic Ointment

Drug Facts

Active ingredient (in each gram)

Bacitracin zinc 400 units

Neomycin sulfate (3.5mg Neomycin)

Polymyxin B sulfate 5000 units

Purpose

First Aid Antibiotics

Uses

First aid to help prevent infection in minor cuts, scrapes and burns

Warnings

For external use only

Do not use

- internally
- in eyes
- over large areas of the body or on puncture wounds, animal bites or serious burns
- for more than 1 week unless directed by a doctor
- if you are allergic to any of the ingredients

Stop use and ask a doctor if

- a rash or other allergic reaction develops
- condition worsens or persists

Keep out of reach of children. If ingested, contact a Poison Control Center right away.

Directions

- clean affected area
- apply a small amount 1 to 3 times daily
- may cover with a sterile bandage

Inactive Ingredients

petrolatum

1% Hydrocortisone Cream

Drug Facts

Active ingredient

Hydrocortisone 1.0%

Purpose

Anti-itch

Uses

- For temporary relief of itching associated with minor skin irritations, inflammation, or rashes.
- Other uses of product should be only under the advice and supervision of a doctor.

Warnings

For external use only

Do not use

- in eyes
- for treatment of diaper rash
- for feminine itching

Stop use, ask a doctor

- if condition worsens or lasts more than 7 days, or clears up and occurs again within a few days
- with use of other hydrocortisone products

Keep out of reach of children. If ingested, contact a Poison Control Center right away

Directions

- apply to affected area not more than 3 to 4 times daily
- children under 2: ask a doctor

Inactive ingredients

emulsifying wax, ethanol, methylparaben, mineral oil, paraffin, petrolatum, propylparaben, purified water, white wax

Instant Hand Sanitizer Gel

Drug Facts

Active ingredient

Ethyl Alcohol 66.5%

Purpose

Antiseptic

Use

For handwashing to decrease bacteria on skin without soap and water.

Warnings

For external use only

Flammable, keep away from fire or flame.

Do not use in eyes, if this happens, rinse thoroughly with water.

Stop use, ask a doctor if, irritation develops and persists for 72 hours.

Keep out of reach of children. If ingested, get medical help or contact a Poison Control Center right away.

Directions

- Wet hands & wrists thoroughly with product and allow to dry without wiping

Inactive ingredients

aloe vera, carbomer, D&C green #5, D&C yellow #10, fragrance, purified water, triethanolamine

FIRST AID TRAVEL KIT

ASSORTED BANDAGES & OINTMENTS

First aid kit sized for travel with everything you'll need and nothing you won't.

- Flexible fabric bandages in two sizes and a few colors to cover cuts and scratches.
- Hand Sanitizer helps keep hands clean when there's no sink in sight.
- Triple Antibiotic ointment helps prevent infection.
- 1% Hydrocortisone anti-itch ointment helps relieve skin irritation and rashes.

Product not made with natural rubber latex.
Bandages are sterile unless individual wrapper opened or damaged.

Distributed by: Welly Health PBC
Minneapolis, MN 55402
1-833-BE-WELLY

Recycle me!

WellyTM www.GetWelly.com

Human Repair Kit

15 BANDAGES - 3/4 x 3 IN (1.9 x 7.6 CM)

15 BANDAGES - 5/8 X 2 1/4 IN (1.6 X 5.7 CM)

3 - TRIPLE ANTIBIOTIC 0.5g (1/57 OZ)

3 - 1% HYDROCORTISONE 0.9g (1/32 OZ)

6 - HAND SANITIZER 0.9g (1/32 OZ)